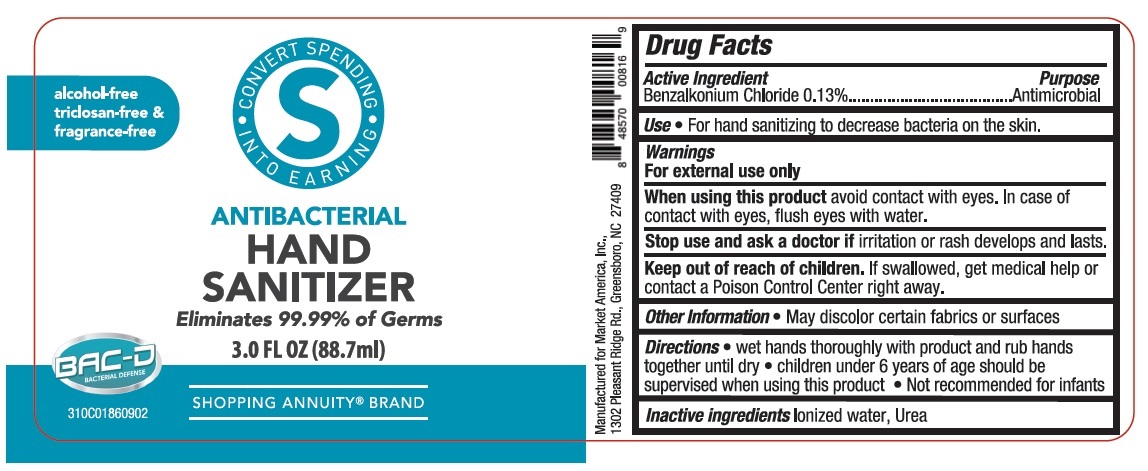 DRUG LABEL: Market America Antibacterial Hand Sanitizer
NDC: 76209-117 | Form: SPRAY
Manufacturer: Market America, Inc.
Category: otc | Type: HUMAN OTC DRUG LABEL
Date: 20210315

ACTIVE INGREDIENTS: BENZALKONIUM CHLORIDE 1.3 mg/1 mL
INACTIVE INGREDIENTS: WATER; UREA

ANTIBACTERIAL HAND SANITIZER

Active Ingredient

Benzalkonium Chloride 0.13%

Purpose

Antimicrobial

Use

• For hand sanitizing to decrease bacteria on the skin.

Warnings

For external use only

When using this product avoid contact with eyes. In case of contact with eyes, flush eyes with water.

Stop use and ask a doctor if irritation or rash develops and lasts.

Keep out of reach of children. If swallowed, get medical help or contact a Poison Control Center right away.

Other Information

• May discolor certain fabrics or surfaces

Directions

• wet hands thoroughly with product and rub hands together until dry. • children under 6 years of age should be supervised when using this product • Not recommended for infants

Inactive ingredients

Ionized water, Urea

CONVERT SPENDING INTO EARNING

alcohol-free

triclosan-free &

fragrance free

Eliminates 99.99% of Germs

SHOPPING ANNUITY® BRAND

BAC-D

BACTERIAL DEFENSE

Manufactured for Market America, Inc.,
1302 Pleasant Ridge Rd., Greensboro, NC 27409